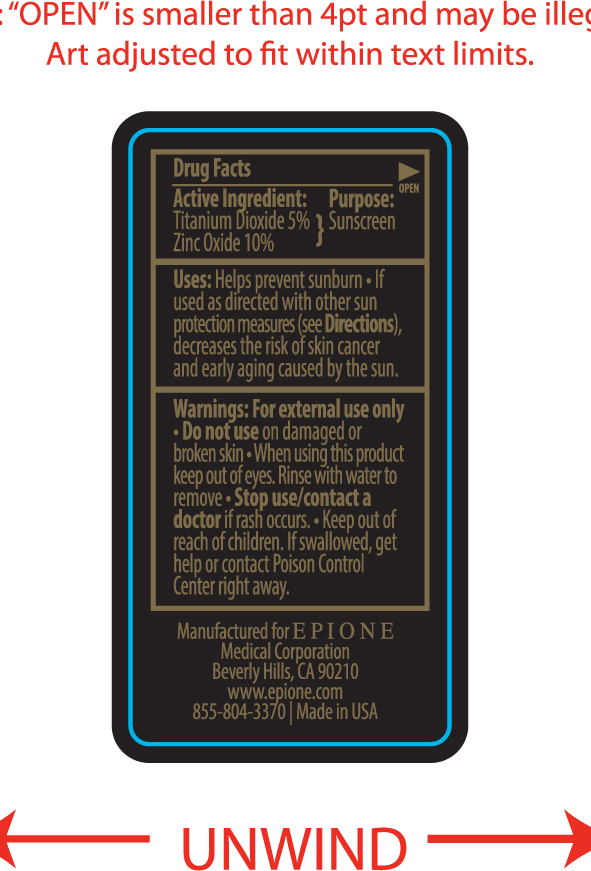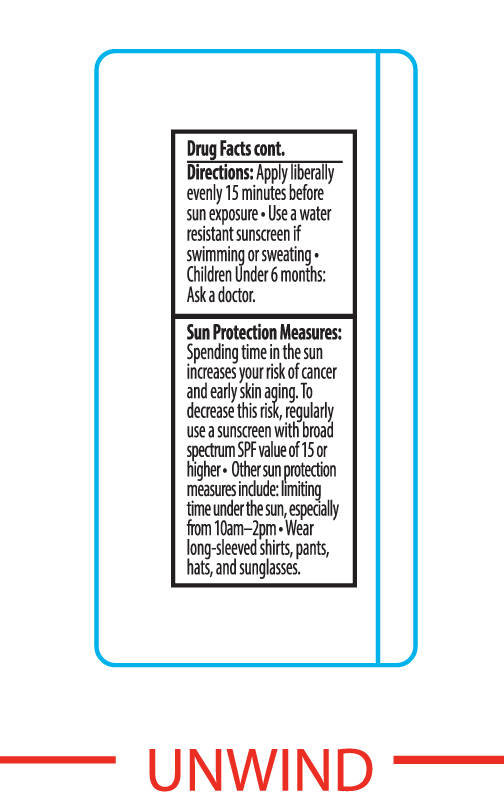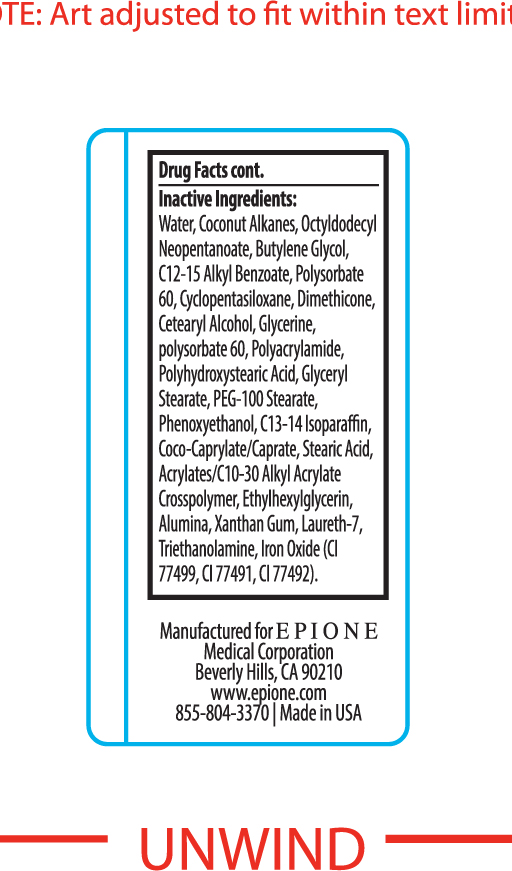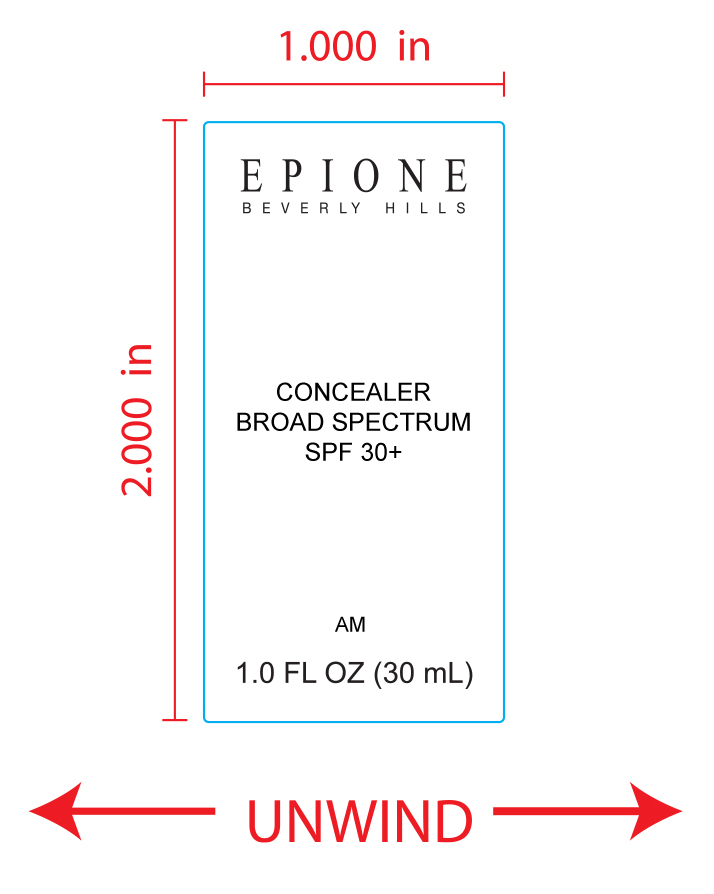 DRUG LABEL: Concealer Broad Spectrum Sunscreen SPF 30
NDC: 70698-004 | Form: CREAM
Manufacturer: Epione Medical Corporation
Category: otc | Type: HUMAN OTC DRUG LABEL
Date: 20180703

ACTIVE INGREDIENTS: TITANIUM DIOXIDE 5 g/100 mL; ZINC OXIDE 10 g/100 mL
INACTIVE INGREDIENTS: WATER; COCONUT ALKANES; OCTYLDODECYL NEOPENTANOATE; BUTYLENE GLYCOL; POLYACRYLAMIDE (1500 MW); PHENOXYETHANOL; ALKYL (C12-15) BENZOATE; XANTHAN GUM; FERROSOFERRIC OXIDE; LAURETH-7; FERRIC OXIDE RED; CYCLOMETHICONE 5; GLYCERIN; POLYHYDROXYSTEARIC ACID (2300 MW); POLYSORBATE 60; DIMETHICONE; CETOSTEARYL ALCOHOL; C13-14 ISOPARAFFIN; ETHYLHEXYLGLYCERIN; FERRIC OXIDE YELLOW; GLYCERYL MONOSTEARATE; PEG-100 STEARATE; COCO-CAPRYLATE/CAPRATE; STEARIC ACID; ALUMINUM OXIDE; TROLAMINE

Concealer Broad Spectrum SPF 30

Active Ingredients:

Titanium Dioxide 5.00%

Zinc Oxide 10.00%

Uses:

Helps prevent sunburn
If used as direct with other sun protection measures (see Directions), decreases the risk of skin cancer and early aging caused by the sun.

Keep out of reach of children. If swallowed, get help or contact a Poison Control Center right away

Stop use/ contact a doctor if rash occurs

Warnings:

For external use only
Do not use on damaged or broken skin
Avoid contact with eyes. Rinse with water to remove

Directions:

Apply evenly 15 minutes before sun exposure
Reapply at least every 2 hours
Use a water resistant sunscreen if swimming or sweating
Children Under 6 months: Ask a doctor.

Sun Protection Measures:

Spending time in the sun increases the risk of skin cancer and early skin aging. To decrease this risk, regularly use a sunscreen with a broad spectrum SPF of 15 or higher and other sun protection measures including:

limit time in the sun, especially from 10a.m.-2p.m.
Wear long-sleeved shirt, pants, hats, and sunglasses
Reapply at least every 2 hours

INACTIVE INGREDIENT

Water, Coconut Alkanes, Octyldodecyl Neopentanoate, Butylene Glycol, C12-15 Alkyl Benzoate, Polysorbate 60, Cyclopentasiloxane, Dimethicone, Cetearyl Alcohol, Glycerine, Polysorbate 60, Polyacrylamide, Polyhydroxystearic Acid, Glyceryl Stearate, PEG-100 Stearate, Phenoxyethanol, C13-14 Isoparaffin, Coco-Caprylate/Caprate, Stearic Acid, Acrylates/C10-30 Alklyl Acrylates Crosspolymer, Ethylhexylglycerin, Alumina, Xanthan Gum, Laureth-7, Triethanolamine, Iron Oxides(CI 77499, CI 77491, CI77492).

PACKAGE LABEL

Epione

Concealer Broad Spectrum SPF 30+

1.0 FL OZ (30mL)